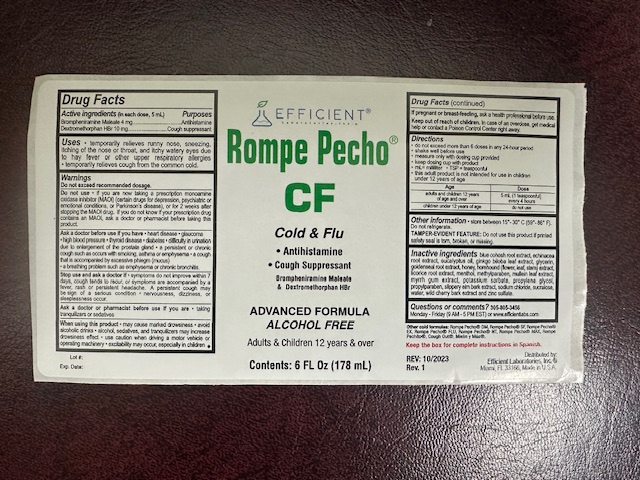 DRUG LABEL: Rompe Pecho CF
NDC: 65852-013 | Form: LIQUID
Manufacturer: Dextrum Laboratories, Inc
Category: otc | Type: HUMAN OTC DRUG LABEL
Date: 20251001

ACTIVE INGREDIENTS: BROMPHENIRAMINE MALEATE 4 mg/5 mL; DEXTROMETHORPHAN HYDROBROMIDE 10 mg/5 mL
INACTIVE INGREDIENTS: HOREHOUND; GINKGO BILOBA LEAF; EUCALYPTUS OIL; CAULOPHYLLUM THALICTROIDES ROOT; LICORICE; GLYCERIN; SODIUM CHLORIDE; SUCRALOSE; WATER; PRUNUS SEROTINA (WILD CHERRY) BARK; ZINC SULFATE; HONEY; ULMUS RUBRA BARK; MENTHOL; ECHINACEA ANGUSTIFOLIA ROOT; GOLDENSEAL; METHYLPARABEN; MULLEIN LEAF; PROPYLENE GLYCOL; PROPYLPARABEN; MYRRH; POTASSIUM SORBATE

Rompe Pecho CF

Active ingredient section

Brompheniramine melate 4mg.... Antihistamine

Dextromethorphan HBr 10 mg... Cough suppressant

Warnings

Do no exceed recommended dosage

Do not use if you are now taking a prescription monoamine oxidase inhibitor(MAOI) (certain drugs for depression, psychiatric or emotional condition, or Parkinson's disease), or 2 weeks after stopping the MAOI drug. If you do not know if your prescription drug contains an MAOI ask a doctor or pharmacist before taking this product.

Ask a doctor section

Ask a doctor before use:

If you have heart disease, glaucoma, high pressure, thyroid disease, diabetes, dificulty in urination due to enlargement of the prostate gland, a persistent or chronic cough such as occurs with smoking, asthma or emphysema, a cough tha is accompanied by excessive phlegm (mucus), a breathing problem such as emphysema or chronic bronchitis.

Ask a doctor and pharmacist section

Ask a doctor/pharmacist section

Ask a doctor or pharmacistbefore use if you are taking tranquilizers or sedatives

Keep out of reach of children section.

In case of a overdose, get medical help or contacta Poison Control Center right away.

Pregnancy or breast feeding section

If pregnancy or breaft-feeding, ask a heath professional before use

Indication and usage section

Do not exceed more than 6 dosesin a 24-hour period

Shake before use

measure only with dosing cup provided

keep dosing cup with product

ml=milliliters TSP=teaspoonful

This adult product is no intented for use in children under 12 years of age

Adult and children 12 years of age and over 5ml (1 teaspoonful) every 4 hours

children under 12 years of age Do not use

Ivactives ingredient section

Blue cohosh root extract, echinacea root extract, eucalyptus oil, ginkgo biloba leaf extract, glycerin, goldenseal root extract, honey, horehound(flower, leaft, stem) extract, licorice root extract, menthol, methylparaben, mullein leaf extract, myrrh gum extract, potassium sorbate, propylene glycol, propylparaben, slippery eilm bark extract, sodium chloride, sucralose, water, wild cherry bark extract and zinc sulfate.

Question section

Question or comments:

305-805-3456

Monday-Friday (9am - 5pm) or www.efficientlabs.com

Purpose section

Antihistaminic

Cough suppressant

Dosage & Administration section

Do not exceed more than 6 dosesin a 24-hour period

Shake before use

measure only with dosing cup provided

keep dosing cup with product

ml=milliliters TSP=teaspoonful

This adult product is no intented for use in children under 12 years of age

Adult and children 12 years of age and over 5ml (1 teaspoonful) every 4 hours

children under 12 years of age Do not use

Principal display panel

Efficient

Rompe Pecho CF

Cold & Flu

Antihistamine

Cough Suppressant

Brompheniramine Melate

Dextromethorphan HBr

Advanced Formula

Alcohol Free

Adults and Children 12 years and over

Content: 6 FL Oz (178 ml)